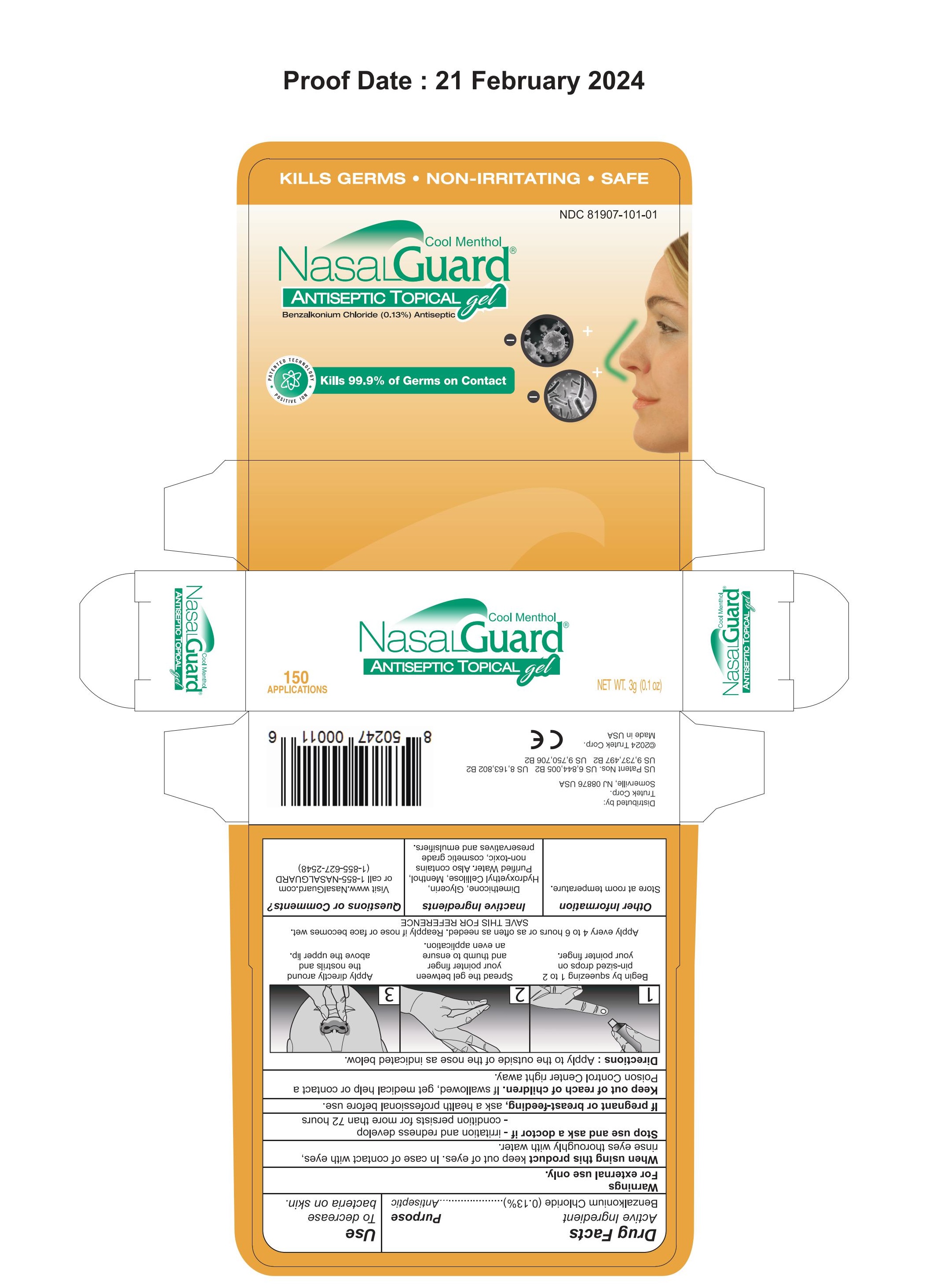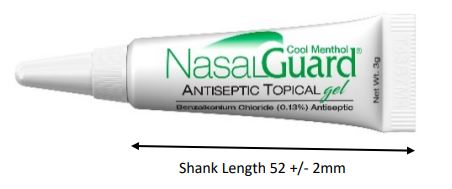 DRUG LABEL: NasalGuard Antiseptic Topical Cool Menthol
NDC: 81907-101 | Form: GEL
Manufacturer: TRUTEK CORP.
Category: otc | Type: HUMAN OTC DRUG LABEL
Date: 20251231

ACTIVE INGREDIENTS: BENZALKONIUM CHLORIDE 1.3 mg/1000 mg
INACTIVE INGREDIENTS: STEARETH-2; MENTHOL; WATER; MEDIUM-CHAIN TRIGLYCERIDES; HYDROXYETHYL CELLULOSE, UNSPECIFIED; STEARETH-21; GLYCERIN; PHENOXYETHANOL; POTASSIUM SORBATE; BEHENTRIMONIUM CHLORIDE; DIMETHICONE 350

NasalGuard Antiseptic Topical Cool Menthol

Active Ingredient

Benzalkonium Chloride 0.13%

Purpose

Antiseptic

Use

To decrease bacteria on the skin.

RECENT MAJOR CHANGES

WARNINGS - NO MAJOR CHANGES. I just saved incomplete, then went in again to complete.

INDICATIONS AND USAGE - Only a date change, not major.

DOSAGE AND ADMINISTRATION - Only a date change, not major.

Directions

Apply to the outside of the nose as indicated below.

Begin by squeezing 1 to 2 pin-sized drops on your pointer finger.

Spread the gel between your pointer finger and thumb to ensure an even application.

Apply directly around the nostrils and above the upper lip.

Apply every 4 to 6 hours or as often as needed.

Reapply if nose or face becomes wet.

SAVE THIS (BOX) FOR REFERENCE

Inactive Ingredients

Dimethicone, Glycerin, Hydroxyethyl Cellulose, Purified Water. Alson contains non-toxic, cosmetic grade preservatives and emulsifiers.

Questions or Comments ?

Visit www.NasalGuard.com or call 1-855-NASALGUARD (1-855-627-2548).

STATEMENT OF IDENTITY

NASALGUARD ANTISEPTIC TOPICAL Gel Cool Menthol

WARNINGS

For external use only

When using this product keep out of eyes. In case of contact with eyes, rinse eyes thoroughly with water.

Stop use and ask a doctor if

irritation and redness develop
condition persists for more than 72 hours

If pregnant or breast-feeding, ask a health professional before use.

Keep out of reach of children. If swallowed, get medical help or contact a Poison Control Center right away.

Keep out of reach of children.

If swallowed, get medical help or contact a Poison Control center right away

Keep out of reach of children. If swallowed, get medical help or contact a Poison Control Center right away.

PREGNANCY OR BREAST FEEDING

If pregnant or breast-feeding, ask a health professional before use.

Stop use and ask a doctor if

irritation and redness develop

or
condition persists for more than 72 hours

PACKAGE LABEL

TUBE AND CARTON FOR MENTHOL NASALGUARD